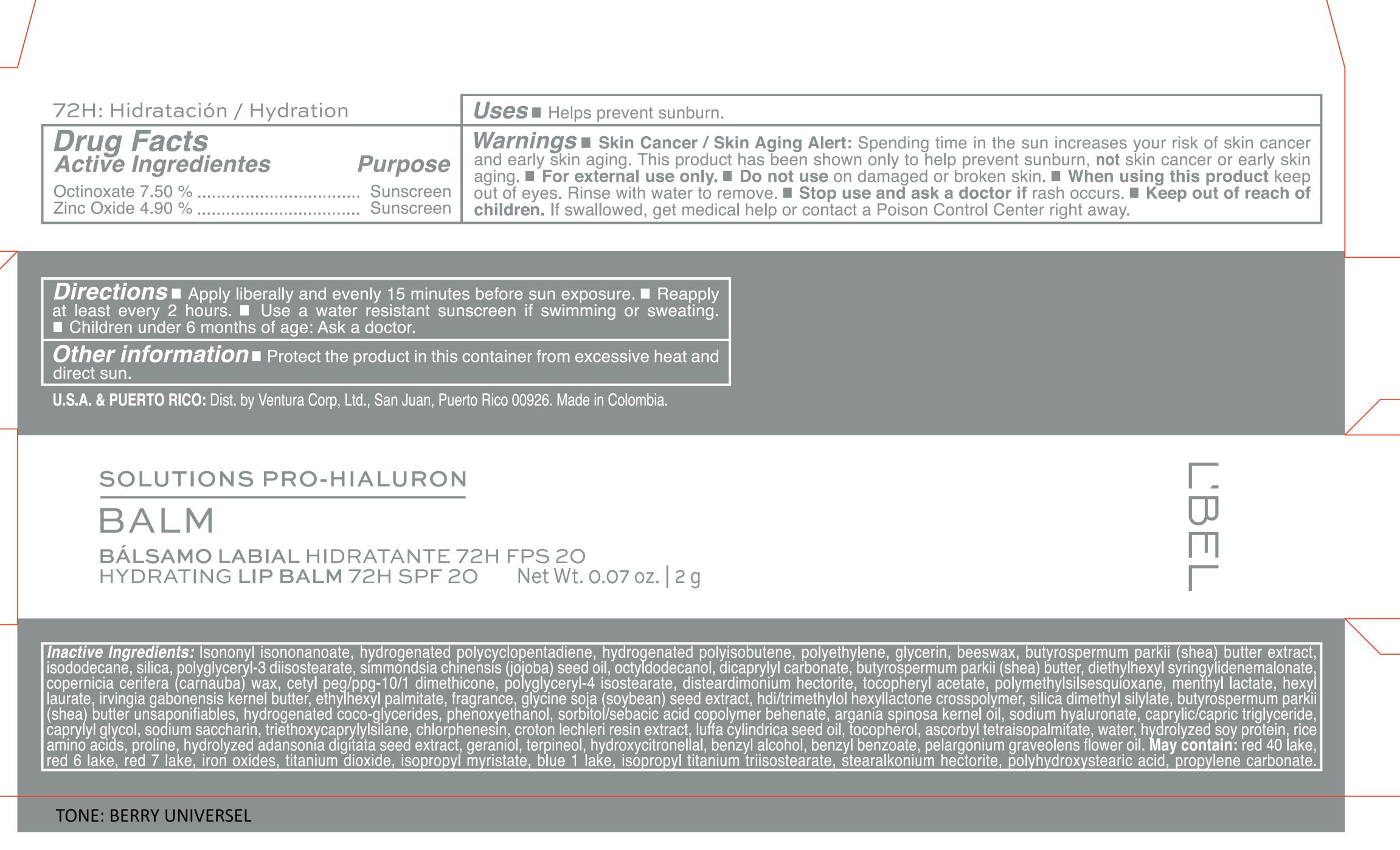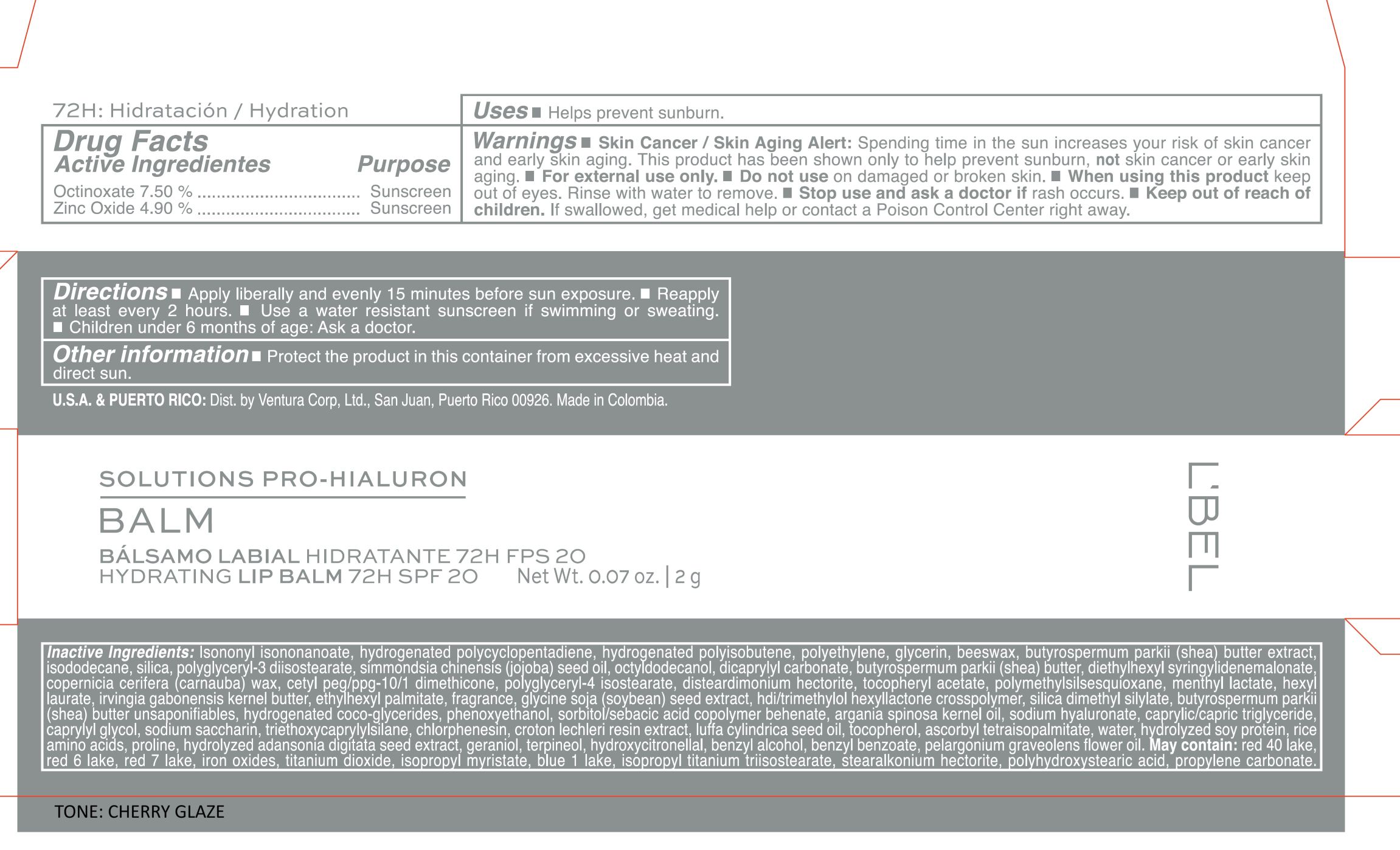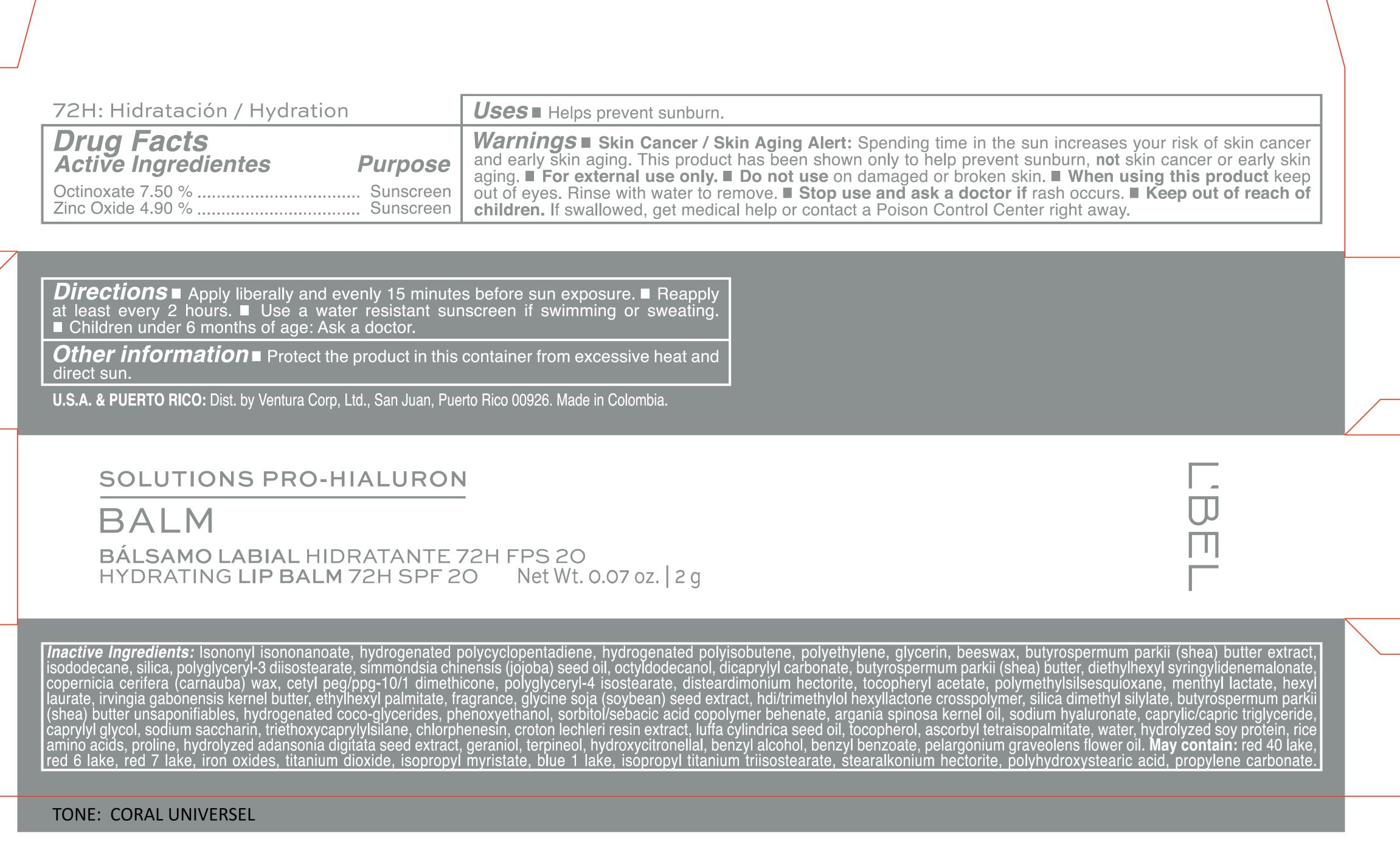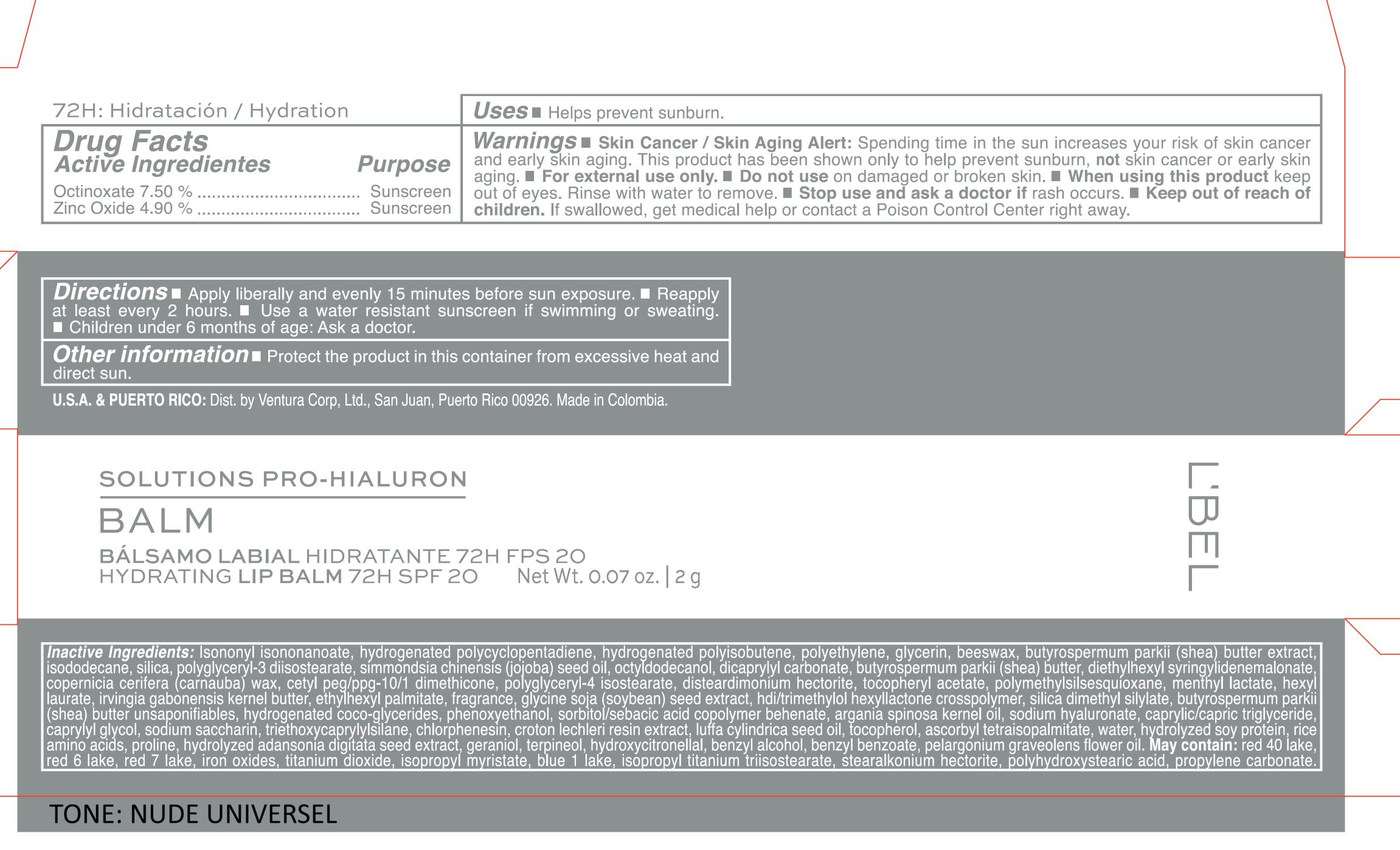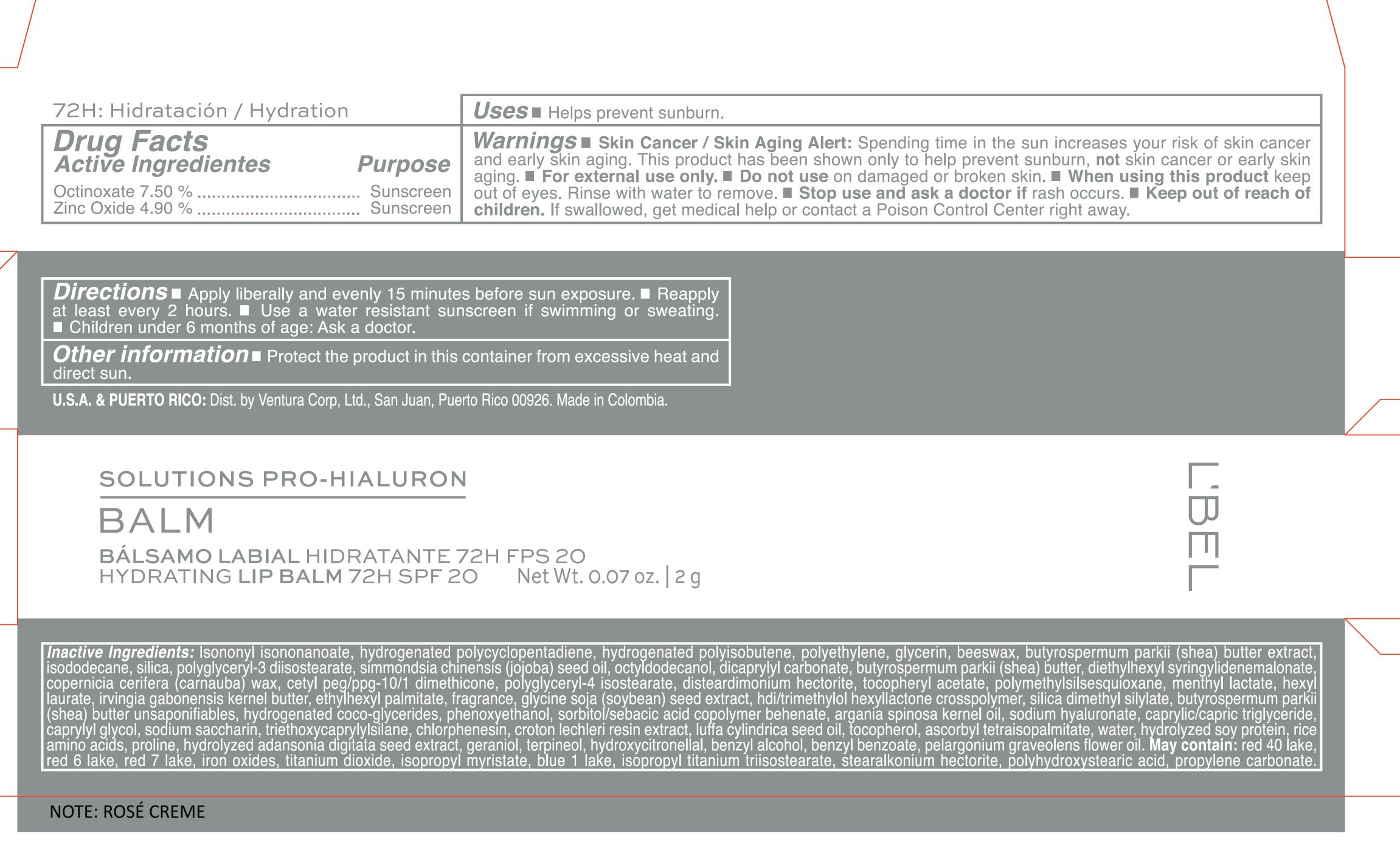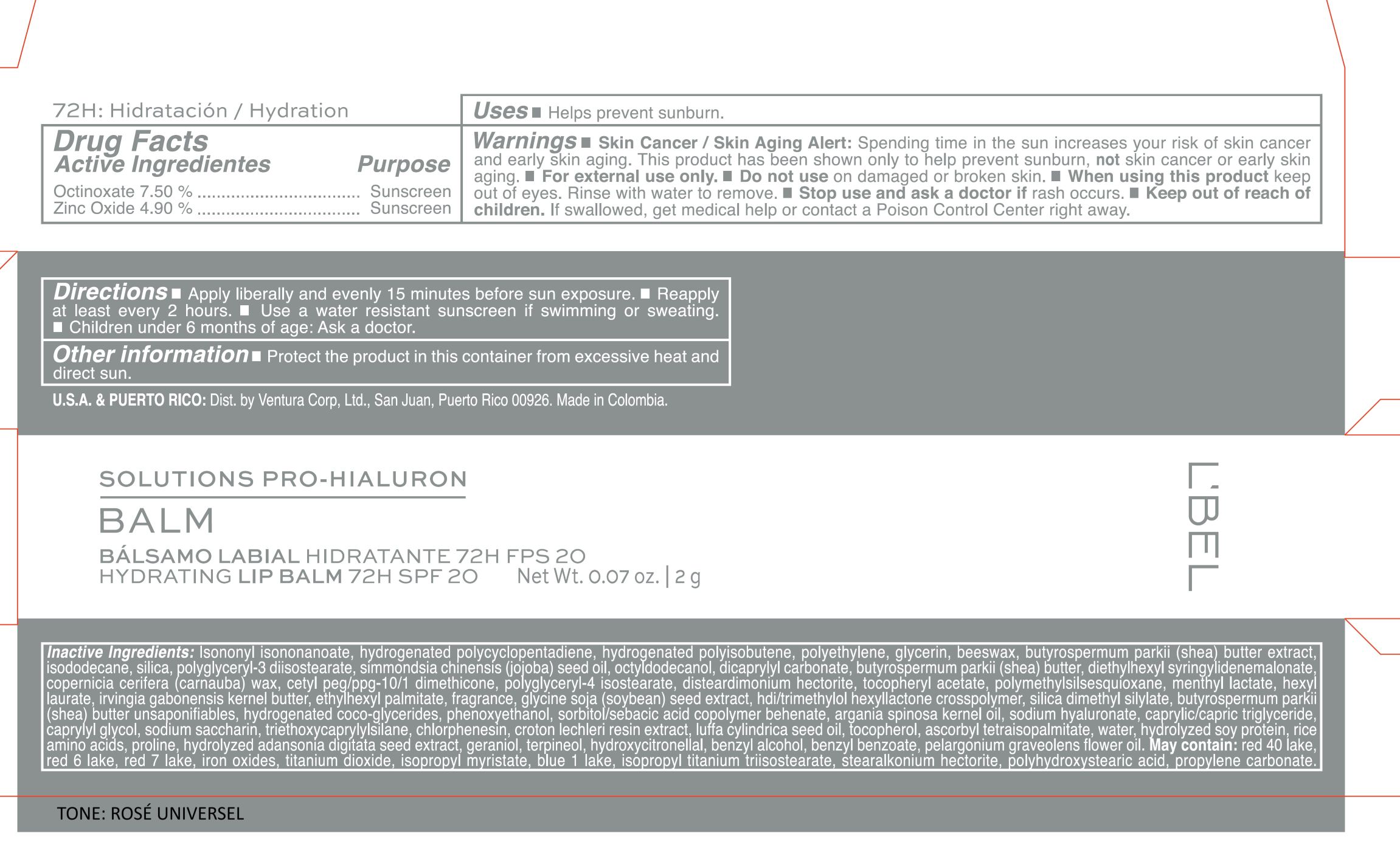 DRUG LABEL: LBEL SOLUTIONS PRO HIALURON BALM BALSAMO LABIAL HIDRATANTE 72H FPS 20 HYDRATING LIP BALM 72H SPF 20 NUDE UNIVERSEL
NDC: 14141-352 | Form: STICK
Manufacturer: BEL STAR S A
Category: otc | Type: HUMAN OTC DRUG LABEL
Date: 20251203

ACTIVE INGREDIENTS: ZINC OXIDE 49 mg/1 g; OCTINOXATE 75 mg/1 g
INACTIVE INGREDIENTS: MENTHYL LACTATE; PROLINE; GLYCERIN; ISONONYL ISONONANOATE; LUFFA CYLINDRICA SEED OIL; RICE AMINO ACIDS; RED 40 LAKE; PROPYLENE CARBONATE; BENZYL ALCOHOL; HYDROGENATED POLYCYCLOPENTADIENE (580 WAMW); CETYL PEG/PPG-10/1 DIMETHICONE (HLB 2); PHENOXYETHANOL; SODIUM HYALURONATE; TOCOPHEROL; STEARALKONIUM HECTORITE; POLYHYDROXYSTEARIC ACID (2300 MW); HDI/TRIMETHYLOL HEXYLLACTONE CROSSPOLYMER; HYDROGENATED COCO-GLYCERIDES; CHLORPHENESIN; CI 77491; POLYETHYLENE; SHEA BUTTER; HEXYL LAURATE; GLYCINE SOJA (SOYBEAN) SEED; SILICA DIMETHYL SILYLATE; IRVINGIA GABONENSIS KERNEL BUTTER; WATER; ETHYLHEXYL PALMITATE; CARNAUBA WAX; POLYMETHYLSILSESQUIOXANE (4.5 MICRONS); TERPINEOL; PELARGONIUM GRAVEOLENS FLOWER OIL; D&C RED NO. 6; TITANIUM DIOXIDE; ISOPROPYL TITANIUM TRIISOSTEARATE; SILICON DIOXIDE; DISTEARDIMONIUM HECTORITE; GERANIOL; HYDROXYCITRONELLAL; BEESWAX; CI 77492; CI 77499; .ALPHA.-TOCOPHEROL ACETATE; BUTYROSPERMUM PARKII (SHEA) BUTTER UNSAPONIFIABLES; CAPRYLIC/CAPRIC TRIGLYCERIDE; CAPRYLYL GLYCOL; ISODODECANE; POLYGLYCERYL-3 DIISOSTEARATE; JOJOBA OIL; OCTYLDODECANOL; SODIUM SACCHARIN; DICAPRYLYL CARBONATE; POLYGLYCERYL-4 ISOSTEARATE; ARGAN OIL; CROTON LECHLERI RESIN; ASCORBYL TETRAISOPALMITATE; HYDROLYZED SOY PROTEIN (ENZYMATIC; 2000 MW); D&C RED NO. 7; TRIETHOXYCAPRYLYLSILANE; ISOPROPYL MYRISTATE; HYDROGENATED POLYISOBUTENE (1300 MW); DIETHYLHEXYL SYRINGYLIDENEMALONATE; CI 42090; BENZYL BENZOATE

LBEL SOLUTIONS PRO HIALURON BALM BALSAMO LABIAL HIDRATANTE 72H FPS 20 HYDRATING LIP BALM 72H SPF 20

Active ingredients

Octinoxate 7.50%

Zinc Oxide 4.90%

Purpose

Sunscreen

Uses

- Helps prevent sunburn.

Warnings

- Skin Cancer/Skin Aging Alert: Spending time in the sun increases your risk of skin cancer and early skin aging. This product has been shown only to help prevent sunburn, not skin cancer or early skin aging.
- For external use only.

Do not use

on damaged or broken skin.

When using this product

keep out of eyes. Rinse with water to remove.

Stop use and ask a doctor if

rash occurs.

Keep out of reach of children.

If swallowed, get medical help or contact a Poison Control Center right away.

Directions

- Apply liberally and evenly 15 minutes before sun exposure
- Reapply at least every 2 hours.
- Use a water resistant sunscreen if swimming or sweating.
- Children under 6 months of age: Ask a doctor.

Other information

- Protect the product in this container ifrom excessive heat and direct sun.

Inactive Ingredients

Isononyl isononanoate, hydrogenated polycyclopentadiene, hydrogenated polyisobutene, polyethylene, glycerin, beeswax, butyrospermum parkii (shea) butter extract, isododecane, silica, polyglyceryl-3 diisostearate, simmondsia chinensis (jojoba) seed oil, octyldodecanol, dicaprylyl carbonate, butyrospermum parkii (shea) butter, diethylhexyl syringylidenemalonate, copernicia cerifera (carnauba) wax, cetyl peg/ppg-10/1 dimethicone, polyglyceryl-4 isostearate, disteardimonium hectorite, tocopheryl acetate, polymethylsilsesquioxane, menthyl lactate, hexyl laurate, irvingia gabonensis kernel butter, ethylhexyl palmitate, fragrance, glycine soja (soybean) seed extract, hdi/trimethylol hexyllactone crosspolymer, silica dimethyl silylate, butyrospermum parkii (shea) butter unsaponifiables, hydrogenated coco-glycerides, phenoxyethanol, sorbitol/sebacic acid copolymer behenate, argania spinosa kernel oil, sodium hyaluronate, caprylic/capric triglyceride, caprylyl glycol, sodium saccharin, triethoxycaprylylsilane, chlorphenesin, croton lechleri resin extract, luffa cylindrica seed oil, tocopherol, ascorbyl tetraisopalmitate, water, hydrolyzed soy protein, rice amino acids, proline, hydrolyzed adansonia digitata seed extract, geraniol, terpineol, hydroxycitronellal, benzyl alcohol, benzyl benzoate, pelargonium graveolens flower oil.

May contain: Red 40 lake, red 6 lake, red 7 lake, iron oxides, titanium dioxide, isopropyl myristate, blue 1 lake, isopropyl titanium triisostearate, stearalkonium hectorite, polyhydroxystearic acid, propylene carbonate.